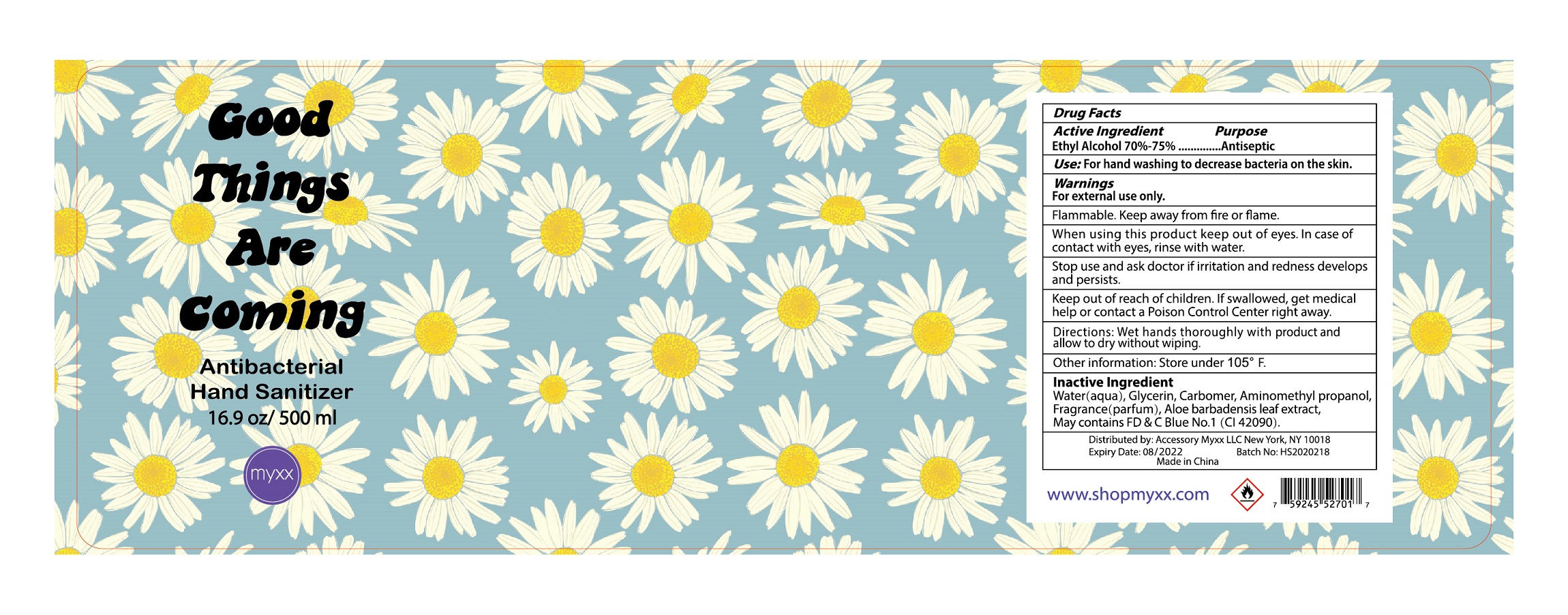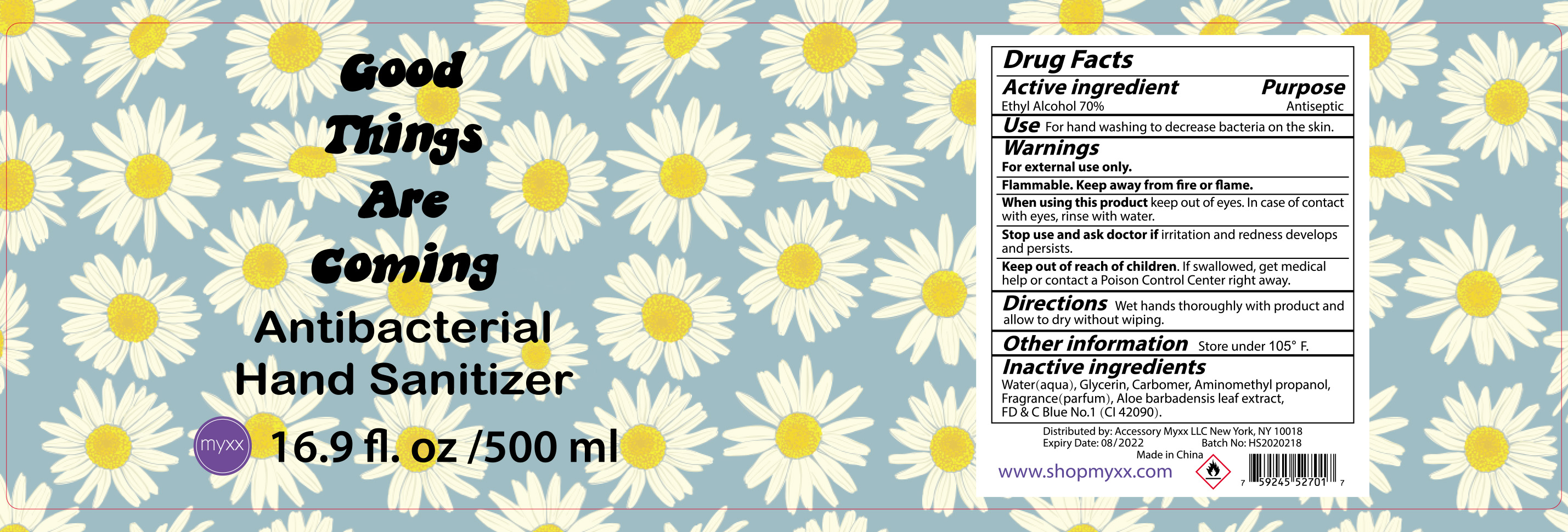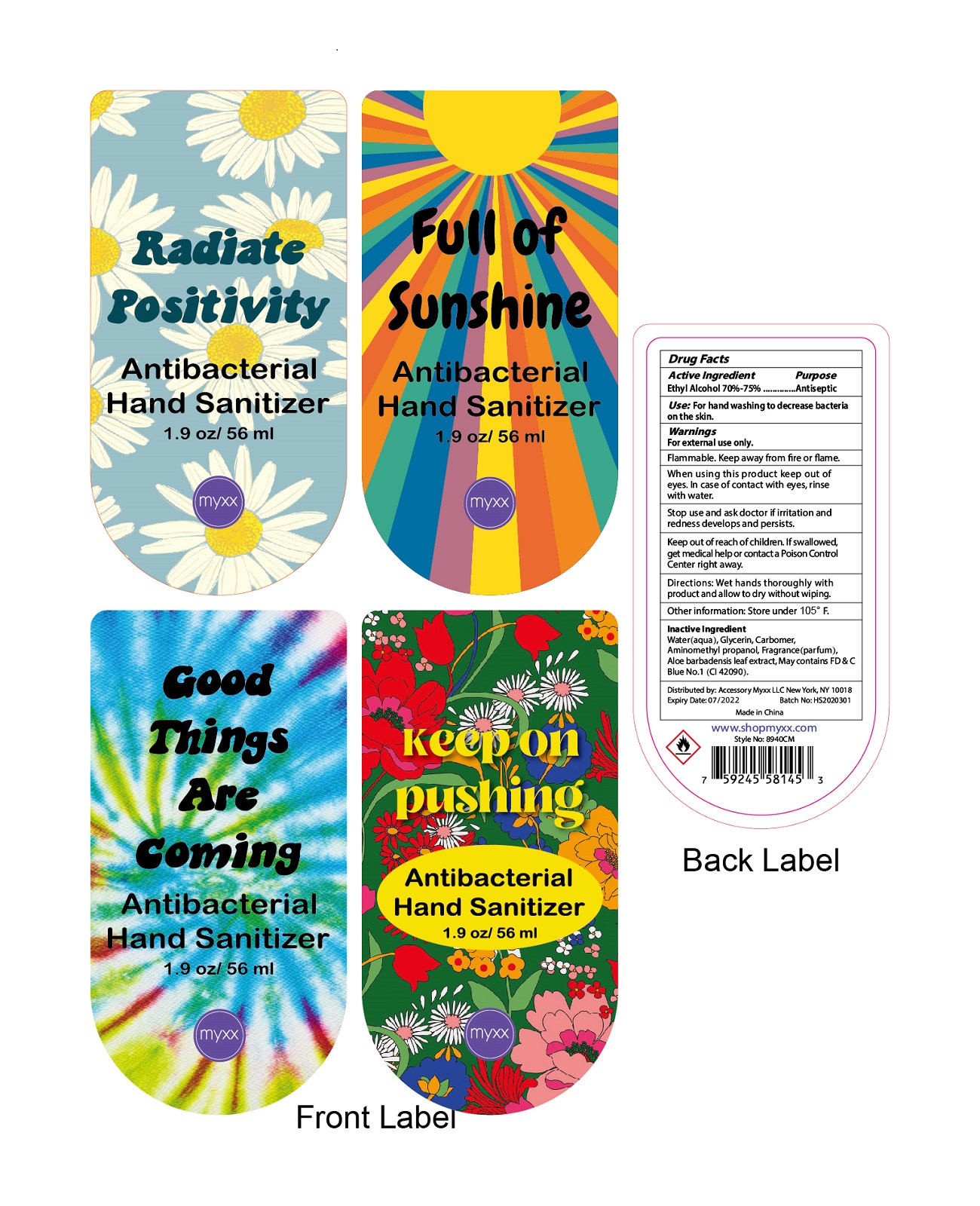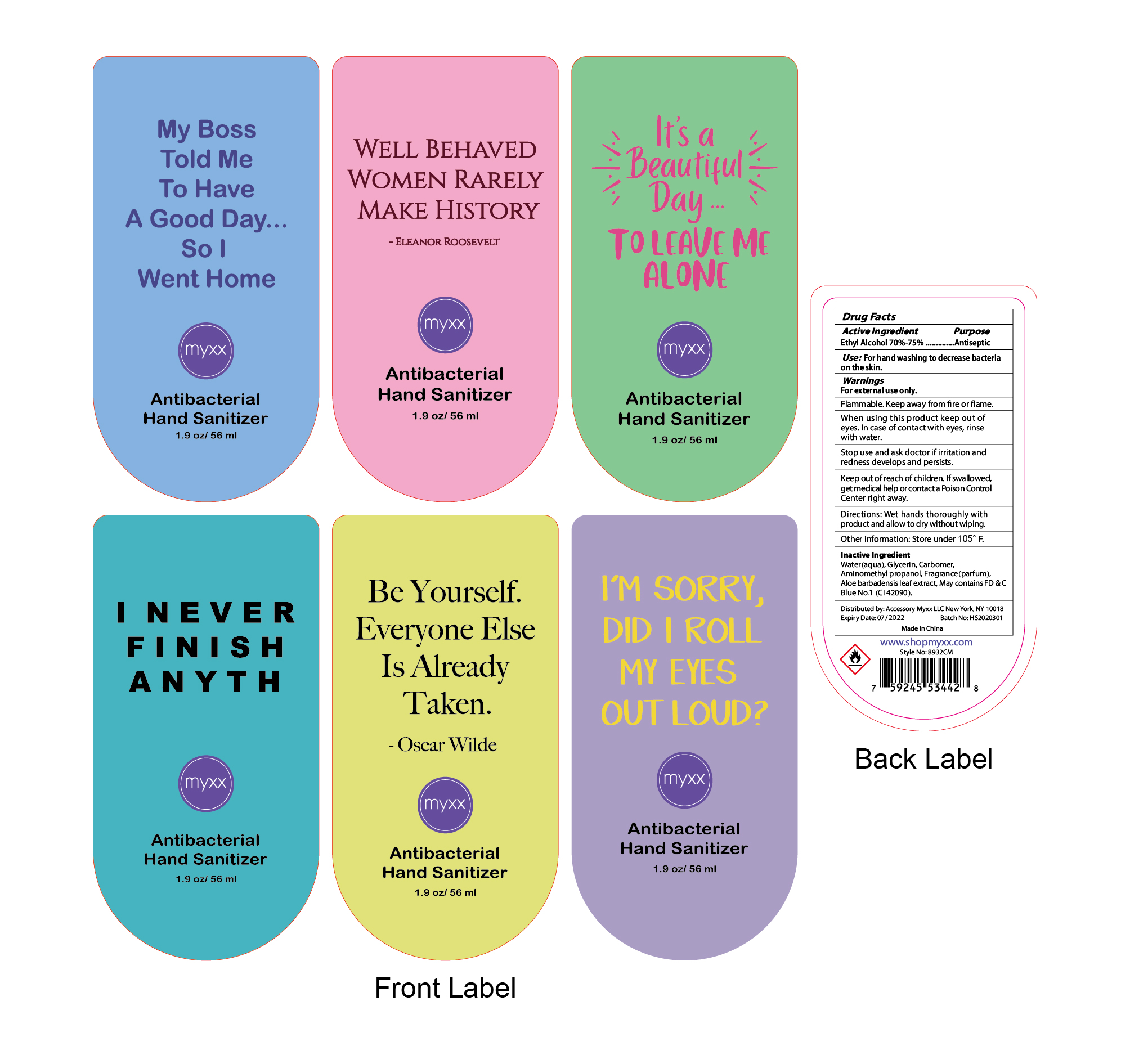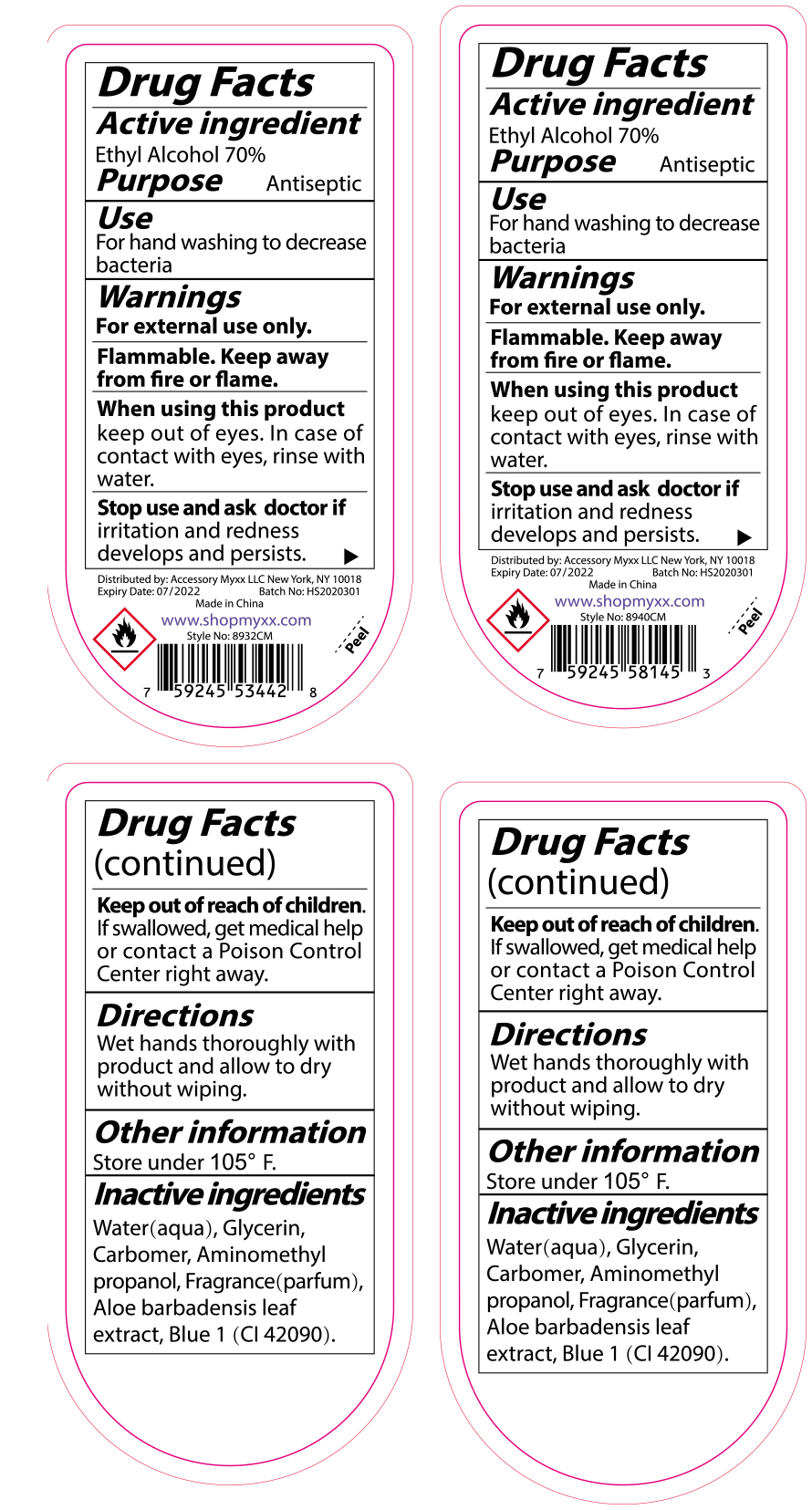 DRUG LABEL: Hand Sanitizer
NDC: 77969-004 | Form: GEL
Manufacturer: Leads (China) Biotechnology Co., Ltd.
Category: otc | Type: HUMAN OTC DRUG LABEL
Date: 20200914

ACTIVE INGREDIENTS: ALCOHOL 70 mL/100 mL
INACTIVE INGREDIENTS: WATER 28.0199 mL/100 mL; CARBOMER 980 0.35 mL/100 mL; AMINOMETHYL PROPANEDIOL 0.18 mL/100 mL; ALOE VERA LEAF 0.05 mL/100 mL; GLYCERIN 1 mL/100 mL; PIGMENT BLUE 1 0.0001 mL/100 mL; FRAGRANCE CLEAN ORC0600327 0.4 mL/100 mL

Hand Sanitizer

ACTIVE INGREDIENT(S)

Ethyl Alcohol 70%-75% v/v. Purpose: Antiseptic

PURPOSE

Antiseptic, Hand Sanitizer

USE

Hand Sanitizer to help reduce bacteria that potentially can cause disease. For use when soap and water are not available.

WARNINGS

For external use only. Flammable. Keep away from heat or flame

DO NOT USE

in children less than 2 months of age
on open skin wounds

WHEN USING

When using this product keep out of eyes, ears, and mouth. In case of contact with eyes, rinse eyes thoroughly with water.
Stop use and ask a doctor if irritation or rash occurs. These may be signs of a serious condition.
Keep out of reach of children. If swallowed, get medical help or contact a Poison Control Center right away.

STOP USE

Stop use and ask a doctor if irritation or rash occurs. These may be signs of a serious condition.

Keep out of reach of children. If swallowed, get medical help or contact a Poison Control Center right away.

DIRECTIONS

Place enough product on hands to cover all surfaces. Rub hands together until dry.
Supervise children under 6 years of age when using this product to avoid swallowing.

OTHER INFORMATION

Store between 15-30C (59-86F)
Avoid freezing and excessive heat above 40C (104F)

INACTIVE INGREDIENTS

Water(aqua), Glycerin, Carbomer, Aminomethyl propanol, Fragrance(parfum), Aloe barbadensis leaf extract, May contains FD & C Blue No.1(CI 42090).

PACKAGE LABEL - PRINCIPAL DISPLAY PANEL

56 mL NDC: 77969-004-01

500 mL NDC: 77969-004-02